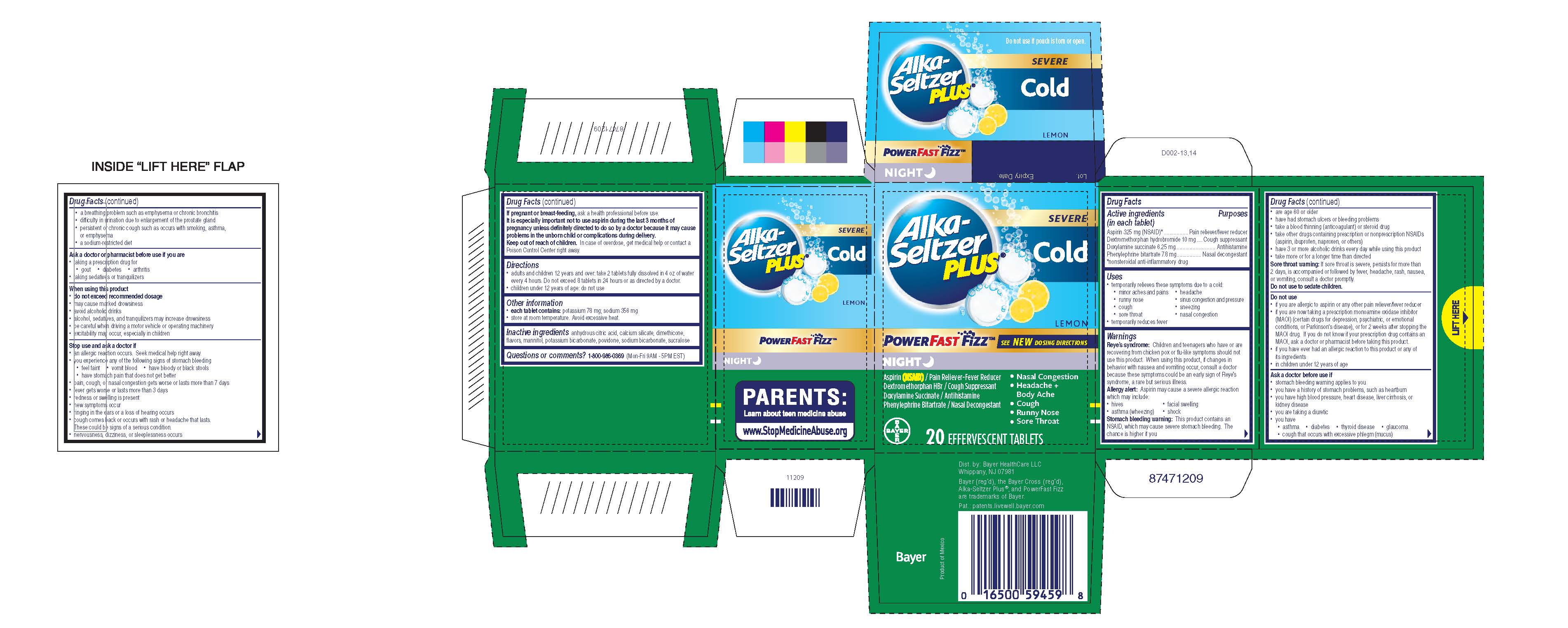 DRUG LABEL: Alka-Seltzer Plus Severe Cold Night PowerFast Fizz
NDC: 0280-0068 | Form: TABLET, EFFERVESCENT
Manufacturer: Bayer HealthCare LLC.
Category: otc | Type: HUMAN OTC DRUG LABEL
Date: 20260108

ACTIVE INGREDIENTS: ASPIRIN 325 mg/1 1; DOXYLAMINE SUCCINATE 6.25 mg/1 1; DEXTROMETHORPHAN HYDROBROMIDE 10 mg/1 1; PHENYLEPHRINE BITARTRATE 7.8 mg/1 1
INACTIVE INGREDIENTS: SODIUM BICARBONATE; ANHYDROUS CITRIC ACID; CALCIUM SILICATE; DIMETHICONE; MANNITOL; POTASSIUM BICARBONATE; POVIDONE; SUCRALOSE

Alka-Selzer Plus Severe Cold PowerFast Fizz Night effervescent tablets UI 1614897

Drug Facts

Active ingredients (in each tablet) Purposes

Aspirin 325 mg (NSAID)*….………………….Pain reliever/fever reducer

Dextromethorphan hydrobromide 10 mg……………Cough suppressant

Doxylamine succinate 6.25 mg…………………………...…Antihistamine

Phenylephrine bitartrate 7.8 mg.......…………….….Nasal decongestant

*nonsteroidal anti-inflammatory drug

Uses

- temporarily relieves these symptoms due to a cold:
  - minor aches and pains
  - headache
  - runny nose
  - sinus congestion and pressure
  - cough
  - sneezing
  - sore throat
  - nasal congestion
- temporarily reduces fever

Warnings
Reye’s syndrome: Children and teenagers who have or are recovering from chicken pox or flu-like symptoms should not use this product. When using this product, if changes in behavior with nausea and vomiting occur, consult a doctor because these symptoms could be an early sign of Reye’s syndrome, a rare but serious illness.
Allergy alert: Aspirin may cause a severe allergic reaction which may include:

- hives
- facial swelling
- asthma (wheezing)
- shock

Stomach bleeding warning: This product contains an NSAID, which may cause severe stomach bleeding. The chance is higher if you

- are age 60 or older
- have had stomach ulcers or bleeding problems
- take a blood thinning (anticoagulant) or steroid drug
- take other drugs containing prescription or nonprescription NSAIDs (aspirin, ibuprofen, naproxen, or others)
- have 3 or more alcoholic drinks every day while using this product
- take more or for a longer time than directed

Sore throat warning: If sore throat is severe, persists for more than 2 days, is accompanied or followed by fever, headache, rash, nausea,or vomiting, consult a doctor promptly.

Do not use to sedate children.

Do not use

- if you are allergic to aspirin or any other pain reliever/fever reducer
- if you are now taking a prescription monoamine oxidase inhibitor (MAOI) (certain drugs for depression, psychiatric, or emotional conditions, or Parkinson's disease), or for 2 weeks after stopping the MAOI drug. If you do not know if your prescription drug contains an MAOI, ask a doctor or pharmacist before taking this product
- if you have ever had an allergic reaction to this product or any of its ingredients
- in children under 12 years of age

Ask a doctor before use if

- stomach bleeding warning applies to you
  - you have a history of stomach problems, such as heartburn
  - you have high blood pressure, heart disease, liver cirrhosis, or kidney disease
  - you are taking a diuretic
  - you have
    - asthma
    - diabetes
    - thyroid disease
    - glaucoma
    - cough that occurs with excessive phlegm (mucus)
    - a breathing problem such as emphysema or chronic bronchitis
    - difficulty in urination due to enlargement of the prostate gland
    - persistent or chronic cough such as occurs with smoking, asthma, or emphysema
    - a sodium-restricted diet

Ask a doctor or pharmacist before use if you are

- taking a prescription drug for
  - gout
  - diabetes
  - arthritis
- taking sedatives or tranquilizers

When using this product

- do not exceed recommended dosage
- may cause marked drowsiness
- avoid alcoholic drinks
- alcohol, sedatives, and tranquilizers may increase drowsiness
- be careful when driving a motor vehicle or operating machinery
- excitability may occur, especially in children

Stop use and ask a doctor if

- an allergic reaction occurs. Seek medical help right away.
- you experience any of the following signs of stomach bleeding
  - feel faint
  - vomit blood
  - have bloody or black stools
  - have stomach pain that does not get better
- pain, cough, or nasal congestion gets worse or lasts more than 7 days
- fever gets worse or lasts more than 3 days
- redness or swelling is present
- new symptoms occur
- ringing in the ears or a loss of hearing occurs
- cough comes back or occurs with rash or headache that lasts. These could be signs of a serious condition.
- nervousness, dizziness, or sleeplessness occurs

PREGNANCY OR BREAST FEEDING

If pregnant or breast-feeding, ask a health professional before use.

It is especially important not to use aspirin during the last 3 months of pregnancy unless definitely directed to do so by a doctor because it may cause problems in the unborn child or complications during delivery.

Keep out of reach of children. In case of overdose, get medical help or contact a Poison Control Center right away.

Directions

● adults and children 12 years and over: take 2 tablets fully dissolved in 4 oz of water every 4 hours. Do not exceed 8 tablets in 24 hours or as directed by a doctor.

● children under 12 years of age: do not use

Other information
● each tablet contains: potassium 78 mg; sodium 356 mg
● store at room temperature. Avoid excessive heat.

INACTIVE INGREDIENT

Inactive ingredients anhydrous citric acid, calcium silicate, dimethicone, flavors, mannitol, potassium bicarbonate, povidone, sodium bicarbonate, sucralose

Questions or comments? 1-800-986-0369 (Mon-Fri 9AM - 5PM EST)

Carton 20 count

Alka-Seltzer Plus®

SEVERE

Cold

LEMON

POWERFAST FIZZ™ SEE NEW DOSING DIRECTIONS

NIGHT

Aspirin (NSAID)/Pain Reliever-Fever Reducer

Dextromethorphan HBr / Cough Suppressant

Doxylamine Succinate / Antihistmine

Phenylephrine Bitartrate / Nasal Decongestant

- Nasal Congestion
- Headache + Body Ache
- Cough
- Runny Nose
- Sore Throat

20 EFFERVESCENT TABLETS